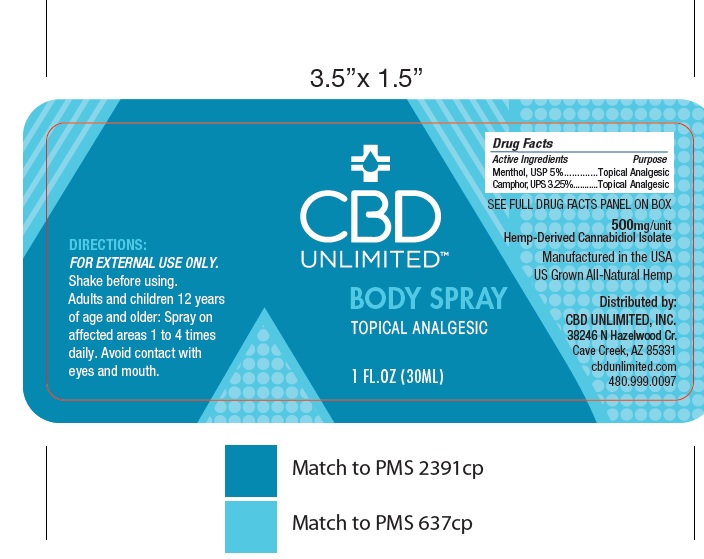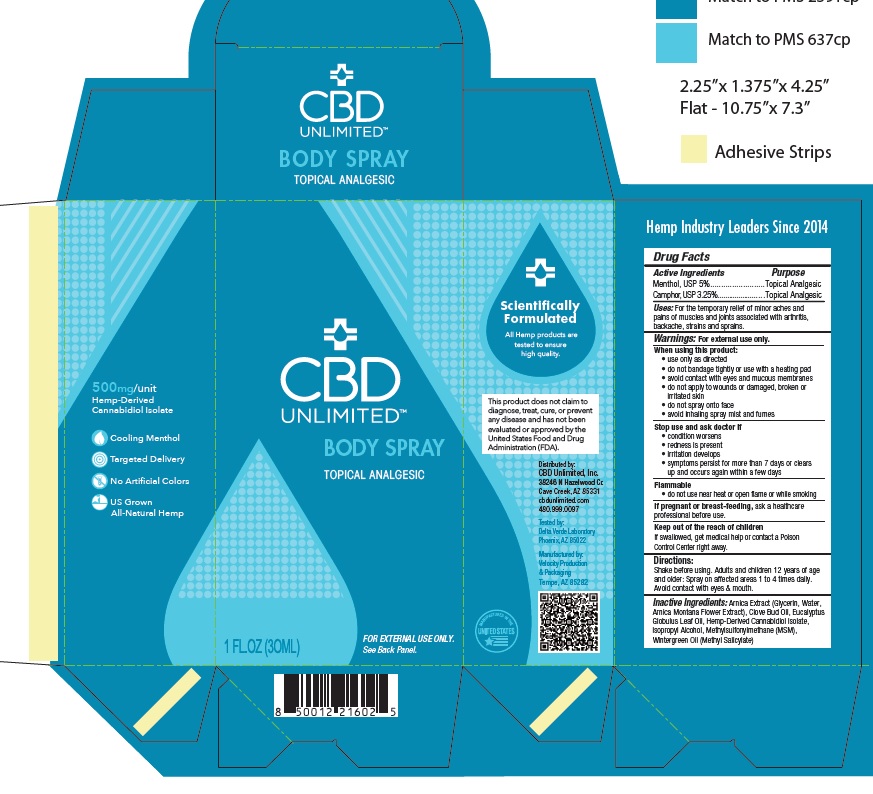 DRUG LABEL: CBD UNLIMITED  TOPICAL ANALGESIC
NDC: 73045-004 | Form: SPRAY
Manufacturer: ENDEXX CORPORATION
Category: otc | Type: HUMAN OTC DRUG LABEL
Date: 20200505

ACTIVE INGREDIENTS: MENTHOL 50 mg/1 mL; CAMPHOR OIL 325 mg/1 mL
INACTIVE INGREDIENTS: ISOPROPYL ALCOHOL; EUCALYPTUS OIL; CLOVE OIL; ARNICA MONTANA FLOWER; Dimethyl Sulfone; GAULTHERIA PROCUMBENS LEAF; Cannabidiol

CBD UNLIMITED BODY SPRAY

Active ingredient

Menthol USP 5%
Camphor 3.25%

Purpose

Topical Analgesic

Uses

Temporary relief from minor aches and pains of muscles & joints associated with: arthritis, simple backache, strains, sprains

Warnings:

For external use only.

When using this product:

• use only as directed
• do not bandage tightly or use with a heating pad
• avoid contact with eyes and mucous membranes
• do not apply to wounds or damaged, broken or irritated skin
• do not spray onto face
• avoid inhaling spray mist and fumes

Stop use and ask doctor if:

• condition worsens
• redness is present
• irritation develops
• symptoms persist for more than 7 days or clears up and occurs again within a few days
Flammable

 do not use near heat or open flame or while smoking

If pregnant or breast-feeding, ask a healthcare professional before use

Keep Out of Reach of Children

If product is swallowed get medical help or contact a Poison Control Center right away.

Directions:

FOR EXTERNAL USE ONLY:

Shake Before Using

Adults and children 12 years of age and older:

Spray on affected areas 1 to 4 times daily.

Avoid contact with eyes and mouth.

Inactive Ingredients

Arnica Extract (Glycerin, Water, Arnica Montana Flower Extract), Clove Bud Oil, Eucalyptus Globulus Leaf Oil, Hemp-Derived Cannabidiol Isolate, Isopropyl Alcohol, Methylsulfonylmethane (MSM), Wintergreen Oil (Methyl Salicylate)